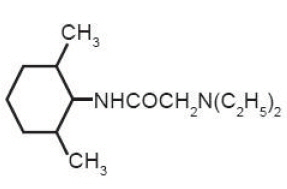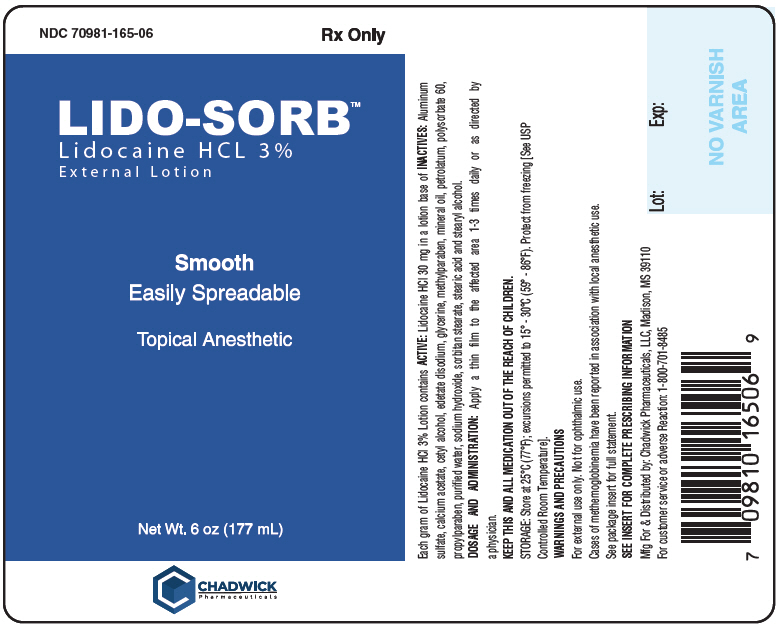 DRUG LABEL: Lido-Sorb External
NDC: 70981-165 | Form: LOTION
Manufacturer: Chadwick Pharmaceuticals, LLC
Category: prescription | Type: HUMAN PRESCRIPTION DRUG LABEL
Date: 20201204

ACTIVE INGREDIENTS: LIDOCAINE HYDROCHLORIDE 30 mg/177 mL
INACTIVE INGREDIENTS: MINERAL OIL; POLYSORBATE 60; SORBITAN MONOSTEARATE; CETYL ALCOHOL; STEARYL ALCOHOL; STEARIC ACID; METHYLPARABEN; PROPYLPARABEN; PETROLATUM; WATER; GLYCERIN; EDETATE DISODIUM; CALCIUM ACETATE; ALUMINUM SULFATE; SODIUM HYDROXIDE

LIDO-SORB™
Lidocaine HCl 3% Lotion

Topical Anesthetic

Rx only

DESCRIPTION

Contains lidocaine HCl 3%. Lidocaine is chemically designated as acetamide, 2-(diethylamino)-N-(2,6- dimethylphenyl), and has the following structure:

C14H22N2O Mol.wt.234 .34

Each gram of Lidocaine HCl 3% Lotion contains ACTIVE: Lidocaine HCl 30 mg in a lotion base of INACTIVES: aluminum sulfate, calcium acetate, cetyl alcohol, edetate disodium, glycerine, methylparaben, mineral oil, petrolatum, polysorbate 60, propylparaben, purified water, sodium hydroxide, sorbitan stearate, stearic acid and stearyl alcohol.

CLINICAL PHARMACOLOGY

MECHANISM OF ACTION

Lidocaine HCl 3% Lotion releases lidocaine which stabilizes the neuronal membrane by inhibiting the ionic fluxes required for initiation and conduction of impulses, thereby effecting local anesthetic action.

PHARMACOKINETICS

Lidocaine may be absorbed following topical administration to mucous membranes, its rate and extent of absorption depending upon the specific site of application, duration of exposure, concentration and total dosage. In general, the rate of absorption of local anesthetic agents following topical application occurs most rapidly after intratracheal administration. Lidocaine is also well-absorbed from the gastrointestinal tract, but little intact drug appears in the circulation because of biotransformation in the liver.

Lidocaine is metabolized rapidly by the liver, and metabolites and unchanged drug are excreted by the kidneys. Biotransformation includes oxidative N-dealkylation, ring hydroxylation, cleavage of the amide linkage, and conjugation. N-dealkylation, a major pathway of biotransformation, yields the metabolites monoethylglycinexylidide and glycinexylidide. The pharmacological / toxicological actions of these metabolites are similar to, but less potent than, those of lidocaine. Approximately 90% of lidocaine administered is excreted in the form of various metabolites, and less than 10% is excreted unchanged. The primary metabolite in urine is a conjugate of 4-hydroxy-2,6-dimethylaniline.

The plasma binding of lidocaine is dependent on drug concentration, and the fraction bound decreases with increasing concentration. At concentrations of 1-4 g of free base per mL, 60 to 80 percent of lidocaine is protein bound. Binding is also dependent on the plasma concentration of the alpha-1-acid glycoprotein.

Lidocaine crosses the blood-brain and placental barriers, presumably by passive diffusion.

Studies of lidocaine metabolism following intravenous bolus injections have shown that the elimination half-life of this agent is typically 1.5 to 2 hours. Because of the rapid rate at which lidocaine is metabolized, any condition that affects liver function may alter lidocaine kinetics. The half-life may be prolonged two-fold or more in patients with liver dysfunction. Renal dysfunction does not affect lidocaine kinetics but may increase the accumulation of metabolites.

Factors such as acidosis and the use of CNS stimulants and depressants affect the CNS levels of lidocaine required to produce overt systemic effects. Objective adverse manifestations become increasingly apparent with increasing venous plasma levels above 6 g free base per mL. In the rhesus monkey, arterial blood levels of 18-21 g/ml have been shown to be threshold for convulsive activity.

INDICATIONS

Pruritus, pruritic eczemas, abrasions, minor burns, insect bites, pain, soreness and discomfort due to pruritus ani, pruritus vulvae, hemorrhoids, anal fissures, and similar conditions of the skin and mucous membranes.

CONTRAINDICAT IONS

Traumatized mucosa, secondary bacterial infection of the area of proposed application and known hypersensitivity to any of the components. Lidocaine is contraindicated in patients with a known history of hypersensitivity to local anesthetics of the amide type.

WARNINGS & PRECAUTIONS

For external use only. Not for ophthalmic use.

If irritation or sensitivity occurs or infection appears, discontinue treatment and institute appropriate therapy. Lidocaine HCl 3% Lotion should be used with caution in ill, elderly, debilitated patients and children who may be more sensitive to the systemic effects of lidocaine.

CARCINOGENESIS, MUTAGENESIS AND IMPAIRMENT OF FERTILITY

Studies of lidocaine in animals to evaluate the carcinogenic and mutagenic potential of the effect on fertility have not been conducted.

METHEMOGLOBINEMIA

Cases of methemoglobinemia have been reported in association with local anesthetic use. Although all patients are at risk for methemoglobinemia, patients with glucose-6-phosphate dehydrogenase deficiency, congenital or idiopathic methemoglobinemia, cardiac or pulmonary compromise, infants under 6 months of age, and concurrent exposure to oxidizing agents or their metabolites are more susceptible to developing clinical manifestations of the condition. If local anesthetics must be used in these patients, close monitoring for symptoms and signs of methemoglobinemia is recommended. Signs and symptoms of methemoglobinemia may occur immediately or may be delayed some hours after exposure and are characterized by a cyanotic skin discoloration and abnormal coloration of the blood. Methemoglobin levels may continue to rise; therefore, immediate treatment is required to avert more serious central nervous system and cardiovascular adverse effects, including seizures, coma, arrhythmias, and death. Discontinue Lidocaine 3% Lotion and any other oxidizing agents. Depending on the severity of the symptoms, patients may respond to supportive care, i.e., oxygen therapy, hydration. More severe symptoms may require treatment with methylene blue, exchange transfusion, or hyperbaric oxygen.

Class | Examples
Nitrates/Nitrites | nitroglycerin, nitroprusside, nitric oxide, nitrous oxide
Local anesthetics | benzocaine, lidocaine, bupivacaine, mepivacaine, tetracaine, prilocaine, procaine, articaine, ropivacaine
Antineoplastic agents | cyclophosphamide, flutamide, rasburicase, ifosfamide, hydroxvurea
Antibiotics | dapsone, sulfonamides, nitrofurantoin, para-aminosalicylic acid
Antimalarials | chloroquine, primaquine
Anticonvulsants | phenvtoin, sodium valoroate, phenobarbital
Other drugs | acetaminophen, metodopramide, sulfa drugs (i.e., sulfasalazine), quinine

DRUG INTERACTIONS

Patients that are administered local anesthetics may be at increased risk of developing methemoglobinemia when concurrently exposed to the following oxidizing agents:

USE IN PREGNANCY

Teratogenic Effects

Pregnancy Category B

Reproduction studies have been performed in rats at doses up to 6.6 times the human dose and have revealed no evidence of harm to the fetus caused by lidocaine. There are, however, no adequate and well controlled studies in pregnant women. Animal reproduction studies are not always predictive of human response. General consideration should be given to this fact before administering lidocaine to women of childbearing potential, especially during early pregnancy when maximum organogenesis takes place.

NURSING MOTHERS

It is not known whether this drug is excreted in human milk. Because many drugs are excreted in human milk, caution should be exercised when this drug is administered to a nursing mother.

PEDIATRIC USE

Dosage in pediatric patients would be reduced commensurate with age, body weight and physical condition.

ADVERSE REACTIONS

During or immediately after treatment, the skin at the site of treatment may develop erythema or edema or maybe the locus of abnormal sensation.

DOSAGE AND ADMINISTRATION

Apply a thin film to the affected area 1 -3 times daily or as directed by a physician.

HOW SUPPLIED

Lidocaine HCl 3% Lotion is supplied in the following size:

SIZE | NDC#
6oz. (177 mL) Bottle | 70981-165-06

KEEP THIS AND ALL MEDICAT ION OUT OF THE REACH OF CHILDREN.

STORAGE

Store at 25°C (77°F); excursions permitted to 15° - 30°C (59° - 86°F). Protect from freezing [See USP Controlled Room Temperature].

Disclaimer: This drug has not been found by FDA to be safe and effective, and this labeling has not been approved by FDA.

Mfg. for & Distributed by: Chadwick Pharmaceuticals, LLC, Madison, MS 39110

For Customer Service or Adverse Reactions: 1-800-701-8485

PRINCIPAL DISPLAY PANEL - 177 mL Bottle Label

NDC 70981-165-06
Rx Only

LIDO-SORB™
Lidocaine HCL 3%
External Lotion

Smooth
Easily Spreadable

Topical Anesthetic

Net Wt. 6 oz (177 mL)

CHADWICK
Pharmaceuticals